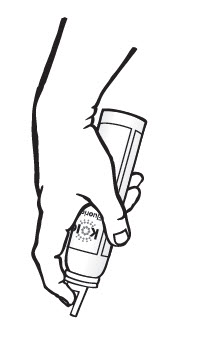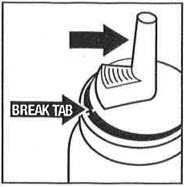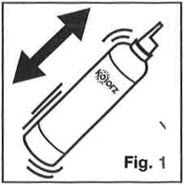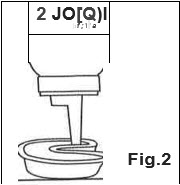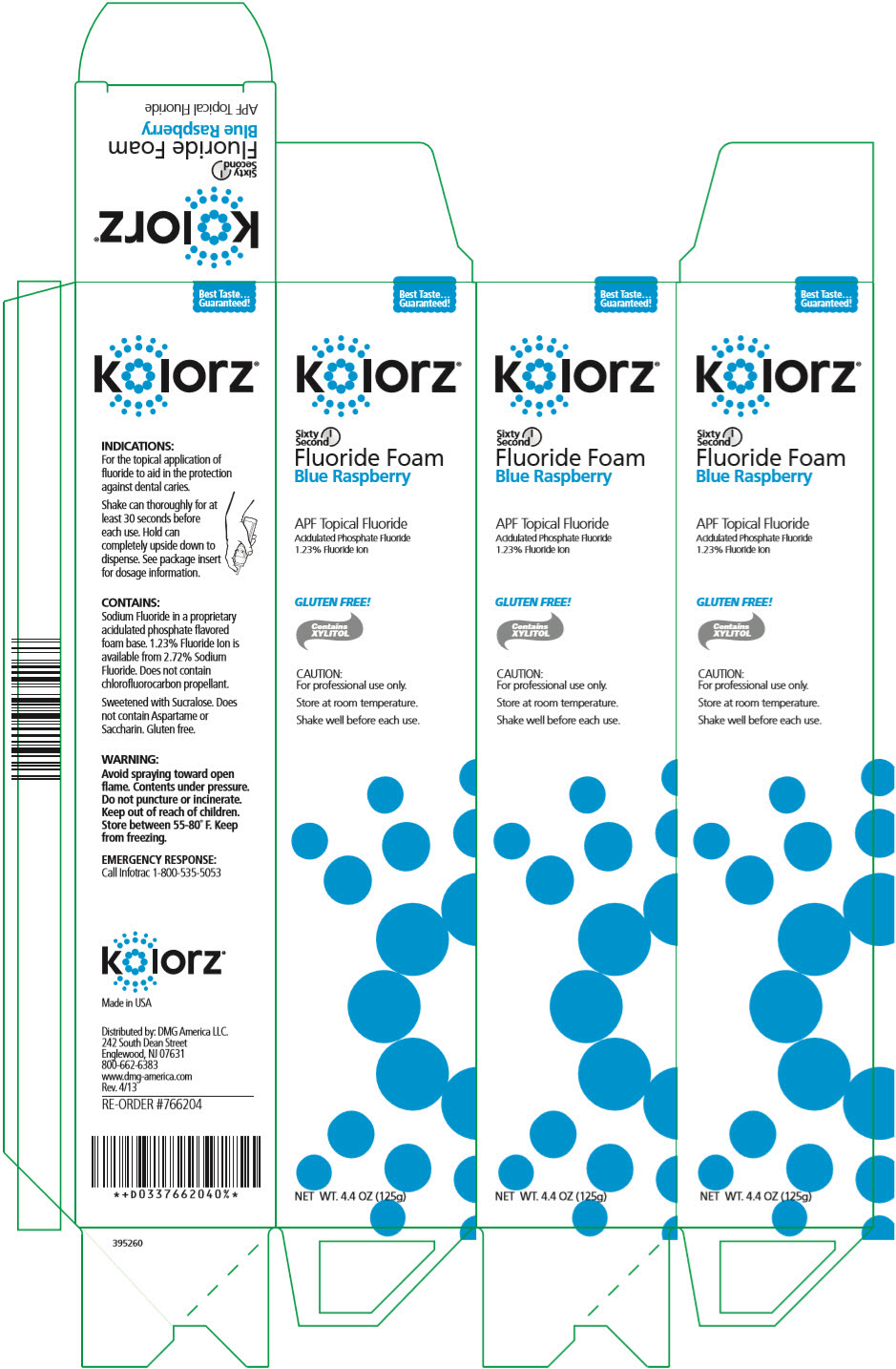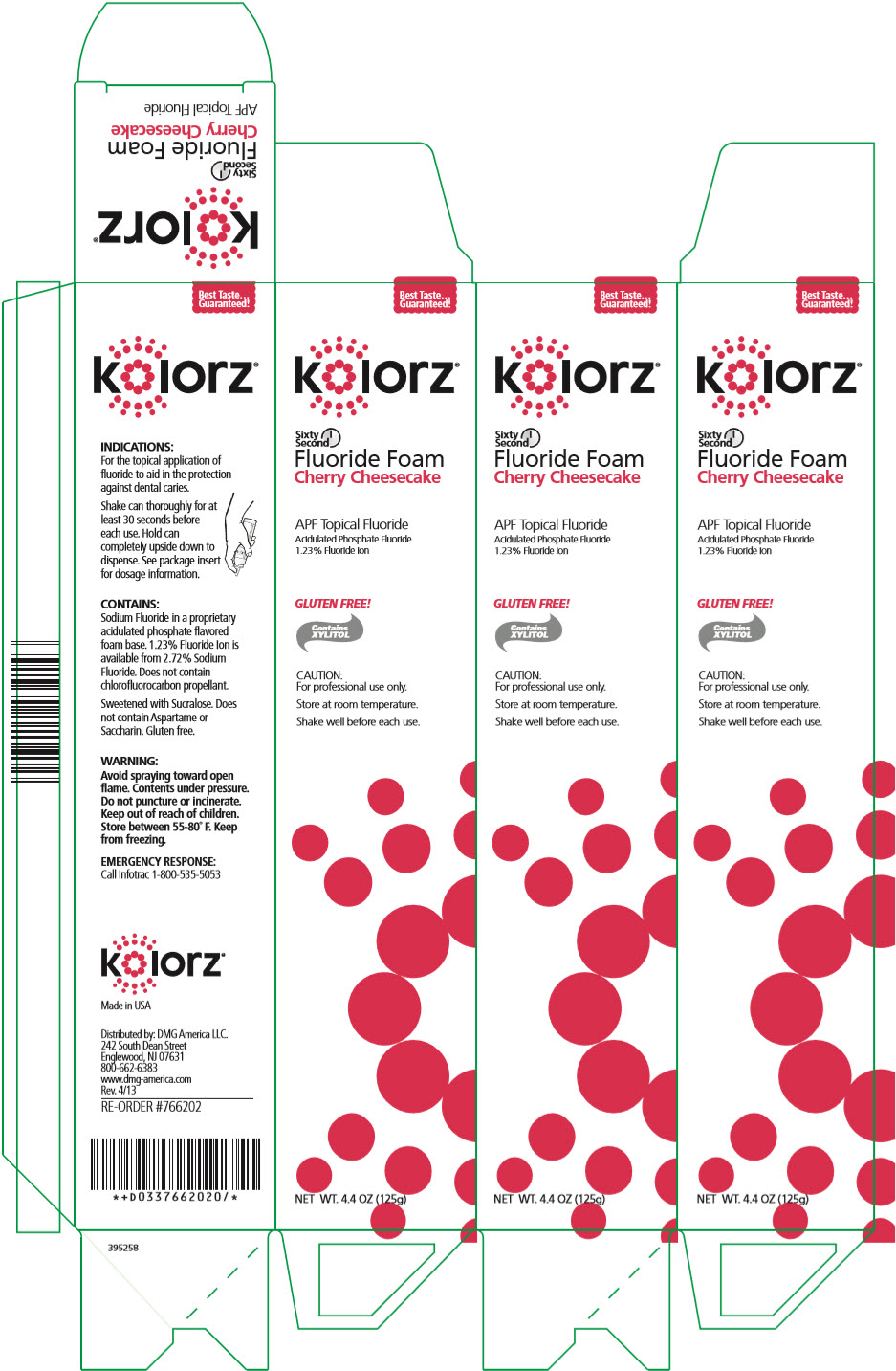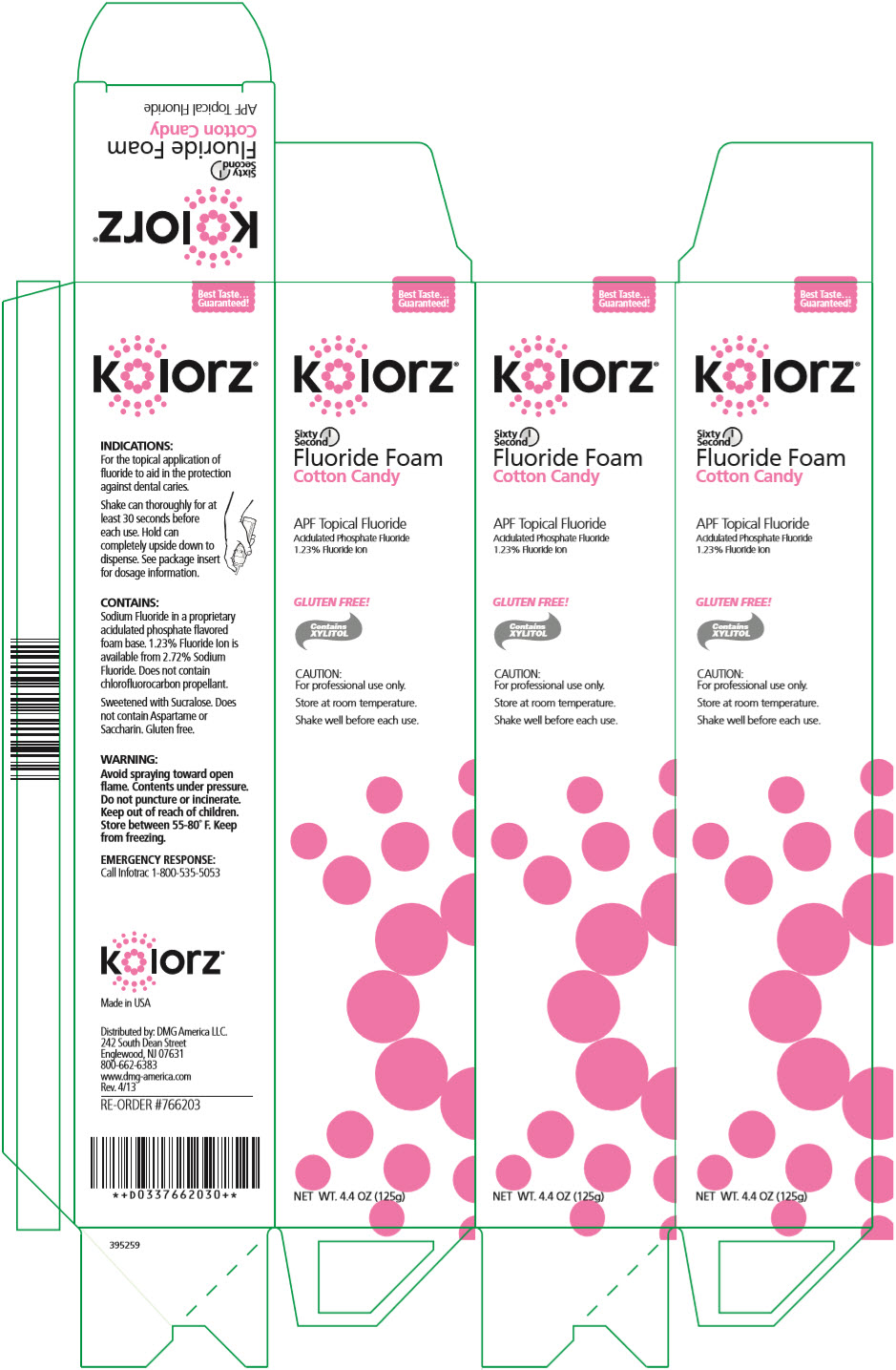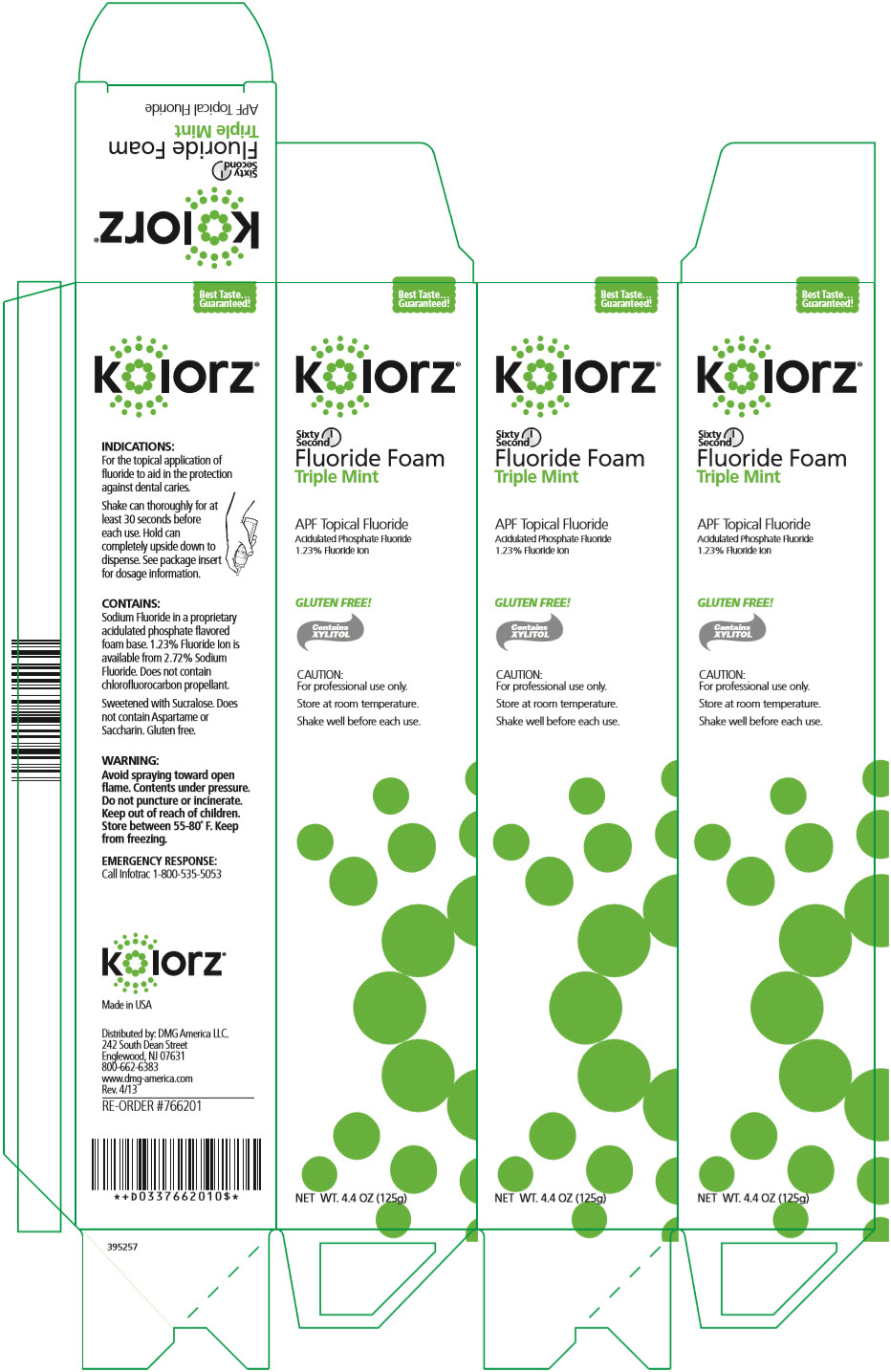 DRUG LABEL: KOLORZ SIXTY SECOND FLUORIDE FOAM 
NDC: 25047-764 | Form: AEROSOL, FOAM
Manufacturer: DMG AMERICA, LLC
Category: prescription | Type: HUMAN PRESCRIPTION DRUG LABEL
Date: 20211001

ACTIVE INGREDIENTS: SODIUM FLUORIDE 1.23 mg/1 g
INACTIVE INGREDIENTS: WATER; SUCRALOSE; XYLITOL; SODIUM PHOSPHATE, MONOBASIC, ANHYDROUS; COCAMIDOPROPYL BETAINE

kolorz® Sixty Second Fluoride Foam

INDICATIONS

For the topical application of fluoride to aid in the protection against dental caries.

Shake can thoroughly for at least 30 seconds before each use. Hold can completely upside down to dispense. See package insert for dosage information.

CONTAINS

Sodium Fluoride in a proprietary acidulated phosphate flavored foam base. 1.23% Fluoride Ion is available from 2.72% Sodium Fluoride. Does not contain chlorofluorocarbon propellant.

Sweetened with Sucralose. Does not contain Aspartame or Saccharin. Gluten free.

WARNING

Avoid spraying toward open flame. Contents under pressure. Do not puncture or incinerate. Keep out of reach of children. Store between 55-80° F. Keep from freezing.

EMERGENCY RESPONSE

Call Infotrac 1-800-535-5053

Made in USA

Distributed by: DMG America LLC.
242 South Dean Street
Englewood, NJ 07631
800-662-6383
www.dmg-america.com
Rev. 4/13

RE-ORDER #766202

INSTRUCTIONS FOR USE

kolorz®

By DMG America
Instructions For Use

Kolorz Sixty Second Fluoride Foam

Kolorz Neutral Fluoride Foam

The first time you dispense from a new bottle, gently lift upward on the nozzle to break the protective shipping tab (thin plastic tab located adjacent to "trigger"). If this tab is not broken, there could be an initial surge of foam from the dispenser.

Dosage and Administration:

1. Shake can vigorously before each use. (Fig. 1)
2. Turn can completely upside down to dispense. Point can towards fluoride applicator tray and slowly press the nozzle to fill tray. Use one press per arch, as foam will expand slightly to fill the tray. (Fig. 2)
3. Dry tooth surface and insert tray(s) in mouth.
4. For Kolorz Sixty Second Fluoride Foam: Have patient bite down lightly but firmly for 1 to 4 minutes; For Kolorz Neutral Fluoride Foam: Have patient bite down lightly but firmly for 4 minutes.
5. Remove tray(s) and have patient expectorate excess
6. Instruct patient not to eat, drink, or rinse for at least 30 minutes after application.

How Supplied: Both Kolorz Sixty Second Fluoride Foam and Kolorz Neutral Fluoride Foam are available in 4.4oz. (125g) cans and do not contain chlorofluorocarbon propellant.

Caution: For professional use only. Federal U.S.A. Law prohibits dispensing without prescription.

Warning: Contents under pressure. Do not puncture or incinerate. Store between 55-80° F. Keep from freezing.

kolorz®

Distributed by DMG America
242 South Dean Street
Englewood, NJ 07631 USA
Tel: 201-894-5505
Fax: 201-894-0213
www.dmg-america.com

395490 Rev. 11/13

PRINCIPAL DISPLAY PANEL - 125 g Can Carton - Blue Raspberry

Best Taste…
Guaranteed!

kolorz®

Sixty
Second
Fluoride Foam
Blue Raspberry

APF Topical Fluoride
Acidulated Phosphate Fluoride
1.23% Fluoride Ion

GLUTEN FREE!

Contains
XYLITOL

CAUTION:
For professional use only.

Store at room temperature.

Shake well before each use.

NET WT. 4.4 OZ (125g)

PRINCIPAL DISPLAY PANEL - 125 g Can Carton - Cherry Cheesecake

Best Taste…
Guaranteed!

kolorz®

Sixty
Second
Fluoride Foam
Cherry Cheesecake

APF Topical Fluoride
Acidulated Phosphate Fluoride
1.23% Fluoride Ion

GLUTEN FREE!

Contains
XYLITOL

CAUTION:
For professional use only.

Store at room temperature.

Shake well before each use.

NET WT. 4.4 OZ (125g)

PRINCIPAL DISPLAY PANEL - 125 g Can Carton - Cotton Candy

Best Taste…
Guaranteed!

kolorz®

Sixty
Second
Fluoride Foam
Cotton Candy

APF Topical Fluoride
Acidulated Phosphate Fluoride
1.23% Fluoride Ion

GLUTEN FREE!

Contains
XYLITOL

CAUTION:
For professional use only.

Store at room temperature.

Shake well before each use.

NET WT. 4.4 OZ (125g)

PRINCIPAL DISPLAY PANEL - 125 g Can Carton - Triple Mint

Best Taste…
Guaranteed!

kolorz®

Sixty
Second
Fluoride Foam
Triple Mint

APF Topical Fluoride
Acidulated Phosphate Fluoride
1.23% Fluoride Ion

GLUTEN FREE!

Contains
XYLITOL

CAUTION:
For professional use only.

Store at room temperature.

Shake well before each use.

NET WT. 4.4 OZ (125g)